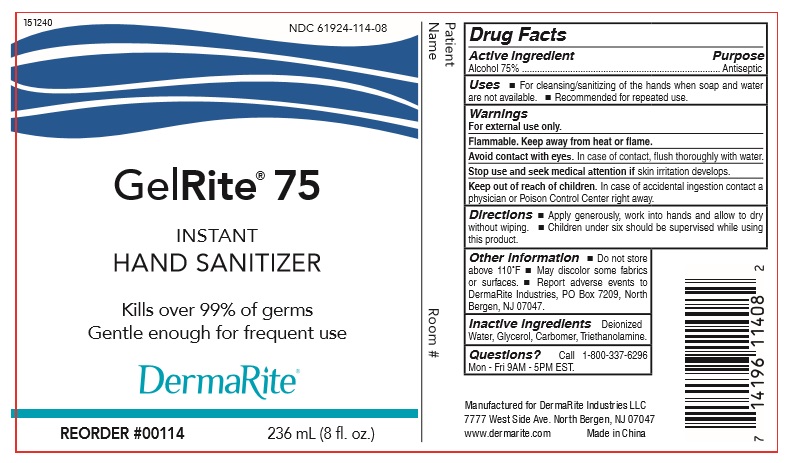 DRUG LABEL: Hand Sanitizer
NDC: 56084-028 | Form: GEL
Manufacturer: Zhejiang RIFESHOW Cosmetics Co., Ltd.
Category: otc | Type: HUMAN OTC DRUG LABEL
Date: 20201113

ACTIVE INGREDIENTS: ALCOHOL 75 mL/100 mL
INACTIVE INGREDIENTS: WATER; CARBOMER 934; GLYCERIN; TROLAMINE

Zhejiang RIFESHOW Cosmetics Co., Ltd.
Hand Sanitizer
236ml 56084-028-01
500ml 56084-028-02

Active Ingredient(s)

Alcohol 75%

Purpose

Antiseptic

Use

- For cleansing/sanitizing of the hands when soap and water are not available.
- Recommended for repeated use.

Warnings

- For external use only.
- Flammable. Keep away from heat or flame.
- Avoid contact with eyes. In case of contact, flush thoroughly with water.

Stop use and seek medical attention if skin irritation develops.

Keep out of reach of children. In case of accidental ingestion contact a physician or Poison Control Center right away.

Directions

- Apply generously, work into hands and allow to dry without wiping.
- Children under six should be supervised while using this product.

Other information

- Do not store above 110℉.
- May discolor some fabrics or surfaces.
- Report adverse events to DermaRite Industries, PO Box 7209, North Bergen, NJ 07047.

Inactive ingredients

Deionized Water, Glycerol, Carbomer, Triethanolamine.

QUESTIONS

Call 1-800-337-6296

Mon-Fri 9AM- 5PM EST.

Package Label - Principal Display Panel

236 mL NDC: 56084-028-01

500 mL NDC: 56084-028-02